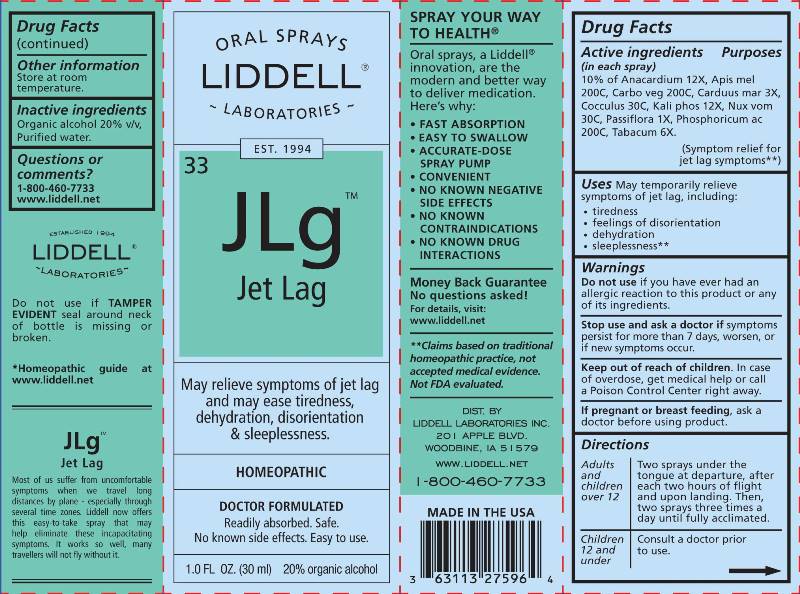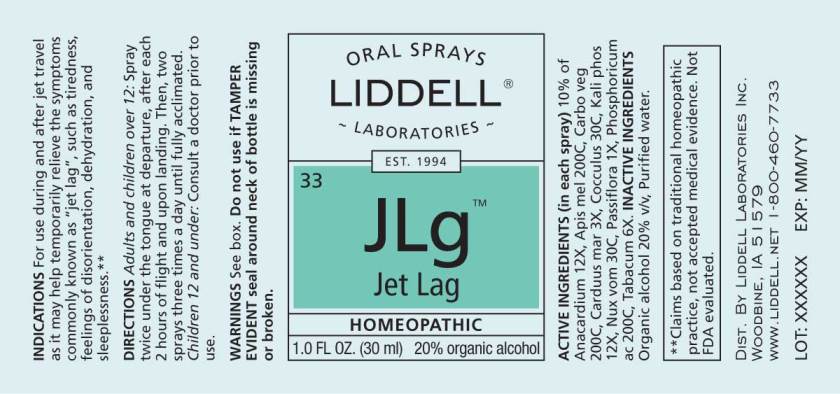 DRUG LABEL: Jet Lag
NDC: 50845-0032 | Form: SPRAY
Manufacturer: Liddell Laboratories, Inc.
Category: homeopathic | Type: HUMAN OTC DRUG LABEL
Date: 20240520

ACTIVE INGREDIENTS: SEMECARPUS ANACARDIUM JUICE 12 [hp_X]/1 mL; APIS MELLIFERA 200 [hp_C]/1 mL; ACTIVATED CHARCOAL 200 [hp_C]/1 mL; SILYBUM MARIANUM SEED 3 [hp_X]/1 mL; ANAMIRTA COCCULUS SEED 30 [hp_C]/1 mL; POTASSIUM PHOSPHATE, DIBASIC 12 [hp_X]/1 mL; STRYCHNOS NUX-VOMICA SEED 30 [hp_C]/1 mL; PASSIFLORA INCARNATA TOP 1 [hp_X]/1 mL; PHOSPHORIC ACID 200 [hp_C]/1 mL; TOBACCO LEAF 6 [hp_X]/1 mL
INACTIVE INGREDIENTS: WATER; ALCOHOL

DRUG FACTS:

ACTIVE INGREDIENTS:

(in each spray): 10% of Anacardium orientale 12X, Apis mellifica 200C, Carbo vegetabilis 200C, Carduus marianus 3X, Cocculus indicus 30C, Kali phosphoricum 12X, Nux vomica 30C, Passiflora incarnata 1X, Phosphoricum acidum 200C, Tabacum 6X.

USES:

May temporarily relieve symptoms of jet lag, including:

- tiredness
- feelings of disorientation
- dehydration
- sleeplessness**

**Claims based upon traditional homeopathic practice, not accepted medical evidence. Not FDA evaluated.

WARNINGS:

Do not use if you have ever had an allergic reaction to this product or any of its ingredients.

Stop use and ask a doctor if symptoms persist for more than 7 days, worsen, or if new symptoms occur.

Keep out of reach of children. In case of overdose, get medical help or call a Poison Control Center right away.

If pregnant or breast-feeding, ask a doctor before using product.

Do not use if TAMPER EVIDENT seal around neck of bottle is missing or broken.

Store at room temperature.

DIRECTIONS:

Adults and children over 12: Two sprays under the tongue at departure, after each two hours of flight and upon landing. Then two sprays three times a day until fully acclimated.

Children 12 and under: Consult a doctor prior to use.

INACTIVE INGREDIENTS:

Organic alcohol 20% v/v, Purified water.

KEEP OUT OF REACH OF CHILDREN:

In case of overdose, get medical help or call a Poison Control Center right away.

USES:

For use during and after jet travel as it may help temporarily relieve the symptoms commonly known as "jet lag", such as tiredness, feelings of disorientation, dehydration, and sleeplessness.**

**Claims based upon traditional homeopathic practice, not accepted medical evidence. Not FDA Evaluated.

QUESTIONS:

DIST. BY

LIDDELL LABORATORIES, INC.

201 APPLE BLVD.

WOODBINE, IA 51579

WWW.LIDDELL.NET

1-800-460-7733

PACKAGE LABEL DISPLAY:

ORAL SPRAYS

LIDDELL

LABORATORIES

EST 1994
^33 JLg

Jet Lag

May relieve symptoms of jet lag

and may ease tiredness,

dehydration, disorientation

& sleeplessness.

HOMEOPATHIC

DOCTOR FORMULATED
Readily absorbed. Safe.

No known side effects. Easy to use

1.0 FL OZ (30 ml)